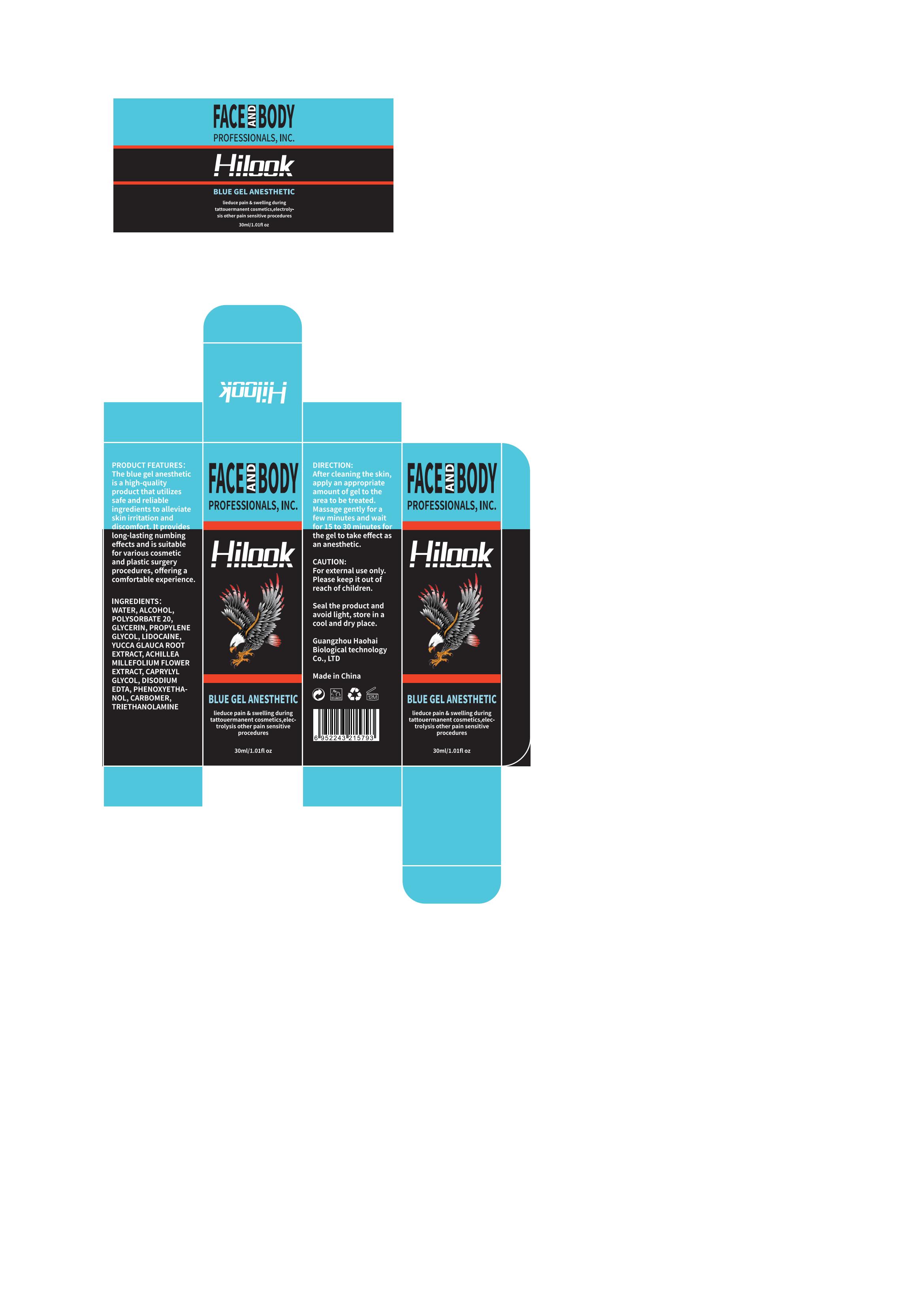 DRUG LABEL: Hilook Blue Gel Anesthetic
NDC: 83566-143 | Form: GEL
Manufacturer: Guangdong Aimu Biological Technology Co., Ltd
Category: otc | Type: HUMAN OTC DRUG LABEL
Date: 20250625

ACTIVE INGREDIENTS: LIDOCAINE 5 g/100 mL
INACTIVE INGREDIENTS: ALCOHOL; GLYCERIN; POLYSORBATE 20

Active ingredients

LIDOCAINE 5%

Purpose

lieduce pain and swelling during tattouermanent cosmetics,electrolysis other pain sensitive procedures

Uses

After cleaning the skin, apply an appropriate amount of gel to the area to be treated.

Massage gently for a few minutes and wait for 15 to 30 minutes for the gel to take effect as an anesthetic.

Warnings

For external use only.

Stop use and ask a doctor if

rash occurs.

Do not use

on damaged or broken skin.

When using this product

keep out of eyes. Rinse with water to remove.

Keep out of reach of children.

If swallowed, get medical help or contact a Poison Control Center right away.

Dosage

Squeeze out an appropriate amount of product and spread evenly on skin.

Inactive ingredients

WATER 36.7%
ALCOHOL 15%
POLYSORBATE 20 3%
GLYCERIN 20%
PROPYLENE GLYCOL 10%
YUCCA GLAUCA ROOT EXTRACT 2%
ACHILLEA MILLEFOLIUM FLOWER EXTRACT 3%
CAPRYLYL GLYCOL 0.3%
DISODIUM EDTA 0.2%
PHENOXYETHA-NOL 0.3%
CARBOMER 3.5%
TRIETHANOLAMINE 1%